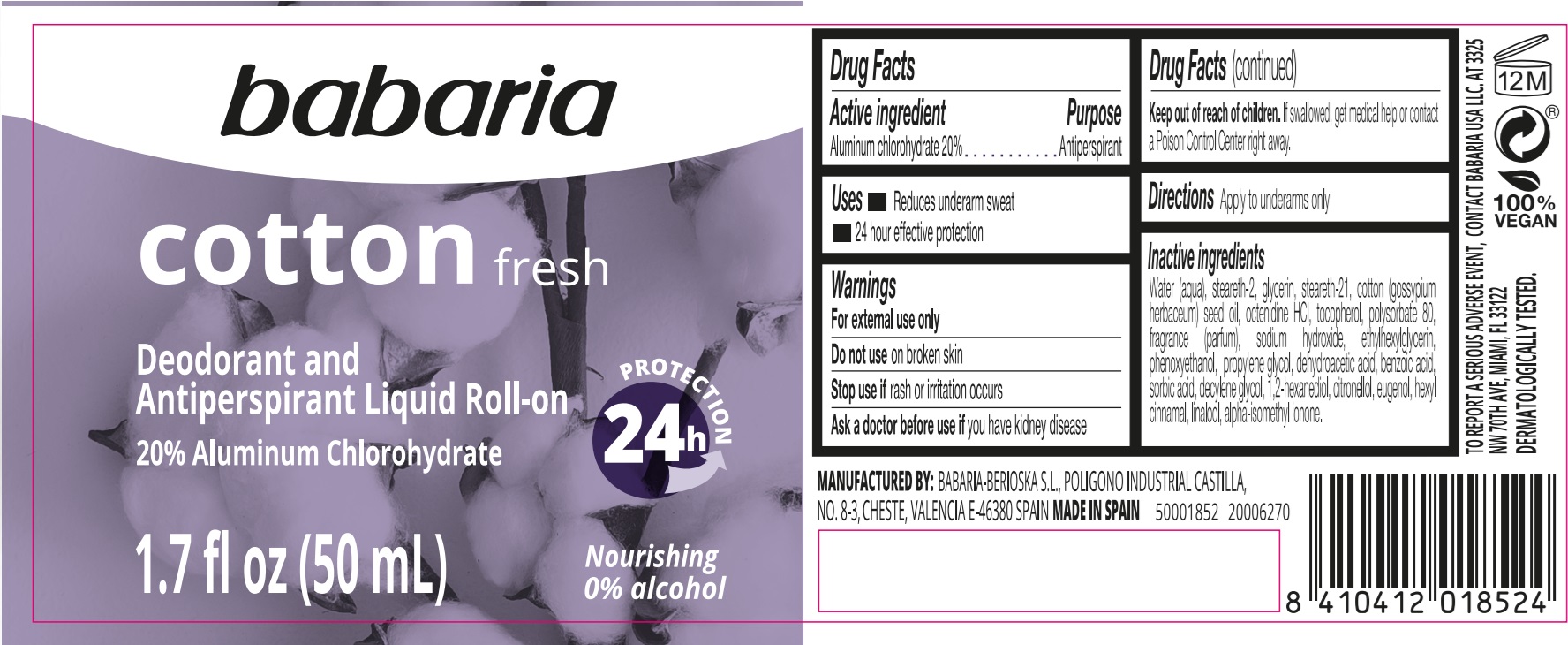 DRUG LABEL: Babaria Cotton Fresh Deodorant and Antiperspirant Liquid Roll-On
NDC: 78283-002 | Form: EMULSION
Manufacturer: BERIOSKA SL
Category: otc | Type: HUMAN OTC DRUG LABEL
Date: 20251220

ACTIVE INGREDIENTS: ALUMINUM CHLOROHYDRATE 200 mg/1 mL
INACTIVE INGREDIENTS: STEARETH-2; WATER; GLYCERIN; STEARETH-21; COTTONSEED OIL; OCTENIDINE HYDROCHLORIDE; TOCOPHEROL; POLYSORBATE 80; SODIUM HYDROXIDE; ETHYLHEXYLGLYCERIN; PHENOXYETHANOL; PROPYLENE GLYCOL; DEHYDROACETIC ACID; BENZOIC ACID; SORBIC ACID; DECYLENE GLYCOL; 1,2-HEXANEDIOL; .BETA.-CITRONELLOL, (R)-; EUGENOL; .ALPHA.-HEXYLCINNAMALDEHYDE; LINALOOL, (+/-)-; ISOMETHYL-.ALPHA.-IONONE

Babaria Cotton Fresh Deodorant and Antiperspirant Liquid Roll-On

Active ingredient

Aluminum chlorohydrate 20%

Purpose

Antiperspirant

Uses

- Reduces underarm sweat
- 24 hour effective protection

Warnings

For external use only

Do not use

on broken skin

Stop use if

rash or irritation occurs

Ask a doctor before use if

you have kidney disease

Keep out of reach of children.

If swallowed, get medical help or contact a Posion Control Center right away.

Directions

Apply to underarms only

Inactive ingredients

Water (aqua), steareth-2, glycerin, steareth-21, cotton (gossypium herbaceum) seed oil, octenidine HCL, tocopherol, Polysorbate 80, fragrance (parfum), sodium hydroxide, ethylhexylglycerin, phenoxyethanol, propylene glycol, dehydroacetic acid, benzoic acid, sorbic acid, decylene glycol, 1,2-hexanediol, citronellol, eugenol, hexyl cinnamal, linalool, alpha-isomethyl ionone.